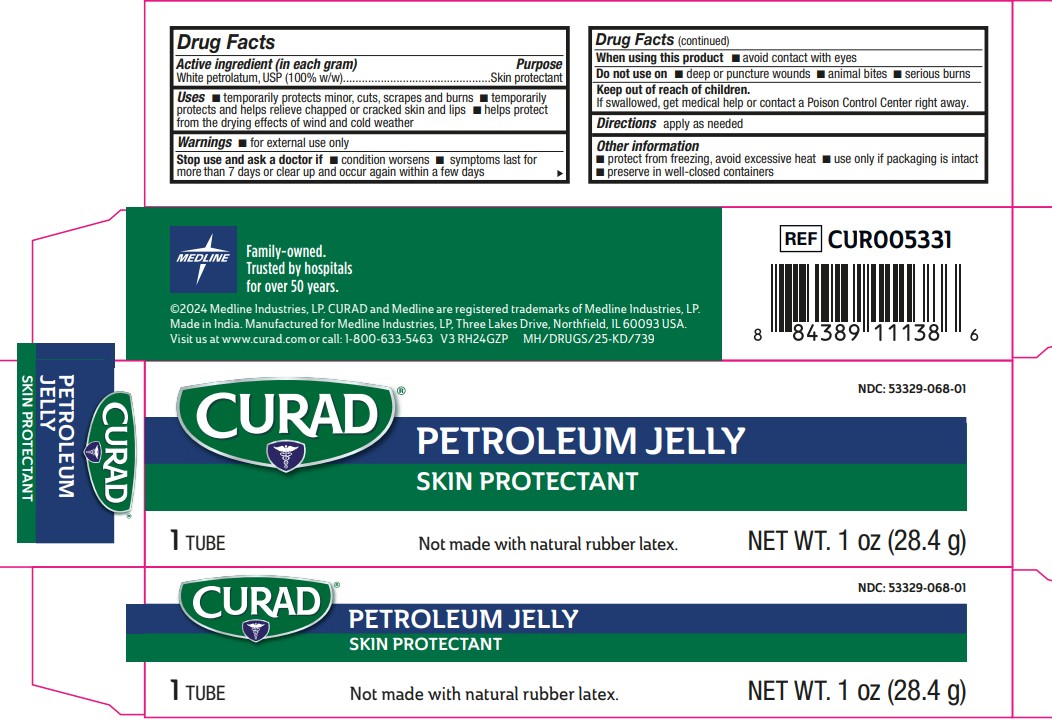 DRUG LABEL: Petroleum
NDC: 53329-068 | Form: JELLY
Manufacturer: Medline Industries, LP
Category: otc | Type: HUMAN OTC DRUG LABEL
Date: 20251009

ACTIVE INGREDIENTS: PETROLATUM 1 g/1 g

068 Curad Petroleum Jelly

Active ingredient (in each gram)

White petrolatum, USP (100% w/w)

Purpose

Skin Protectant

Uses

- temporarily protects minor: cuts, scrapes and burns
- temporarily protects and helps relieve chapped or cracked skin and lips
- helps protect from the drying effects of wind and cold weather

Warnings

- For external use only

Do not use on

- deep or puncture wounds
- animal bites
- serious burns

When using this product

- avoid contact with eyes

Stop use and ask a doctor if

- condition worsens
- symptoms last for more than 7 days or clear up and occur again within a few days

KEEP OUT OF REACH OF CHILDREN.

If swallowed, get medical help or contact a Poison Control Center right away.

Directions

apply as needed.

Other information

- protect from freezing, avoid excessive heat
- Use only if packaging is intact.
- preserve inb well-closed containers

Manufacturing Information

Manufactured for:

Medline Industries, LP

Three Lakes Drive, Northfield, IL 60093 USA

Made in USA of Domestic and Imported Materials

www.curad.com

1-800-633-5463

REF: CUR005331

Inactive ingredients

N/A